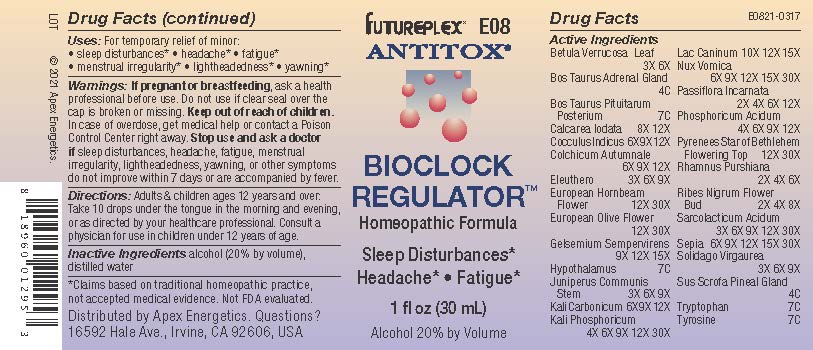 DRUG LABEL: E08
NDC: 63479-0508 | Form: SOLUTION/ DROPS
Manufacturer: Apex Energetics Inc.
Category: homeopathic | Type: HUMAN OTC DRUG LABEL
Date: 20240108

ACTIVE INGREDIENTS: CARPINUS BETULUS FLOWER 30 [hp_X]/1 mL; OLEA EUROPAEA FLOWER 30 [hp_X]/1 mL; GELSEMIUM SEMPERVIRENS ROOT 15 [hp_X]/1 mL; ANAMIRTA COCCULUS SEED 12 [hp_X]/1 mL; BOS TAURUS HYPOTHALAMUS 7 [hp_C]/1 mL; JUNIPERUS COMMUNIS STEM 9 [hp_X]/1 mL; PHOSPHORIC ACID 12 [hp_X]/1 mL; LACTIC ACID, L- 30 [hp_X]/1 mL; SEPIA OFFICINALIS JUICE 30 [hp_X]/1 mL; POTASSIUM CARBONATE 12 [hp_X]/1 mL; POTASSIUM PHOSPHATE, DIBASIC 30 [hp_X]/1 mL; TYROSINE 7 [hp_C]/1 mL; SOLIDAGO VIRGAUREA FLOWERING TOP 9 [hp_X]/1 mL; ORNITHOGALUM UMBELLATUM FLOWERING TOP 30 [hp_X]/1 mL; FRANGULA PURSHIANA BARK 6 [hp_X]/1 mL; PASSIFLORA INCARNATA TOP 12 [hp_X]/1 mL; SUS SCROFA PINEAL GLAND 4 [hp_C]/1 mL; BETULA PENDULA LEAF 6 [hp_X]/1 mL; CALCIUM IODIDE 12 [hp_X]/1 mL; CANIS LUPUS FAMILIARIS MILK 15 [hp_X]/1 mL; BOS TAURUS ADRENAL GLAND 4 [hp_C]/1 mL; BOS TAURUS PITUITARY GLAND 7 [hp_C]/1 mL; RIBES NIGRUM FLOWER BUD 8 [hp_X]/1 mL; TRYPTOPHAN 7 [hp_C]/1 mL; ELEUTHERO 9 [hp_X]/1 mL; STRYCHNOS NUX-VOMICA SEED 30 [hp_X]/1 mL; COLCHICUM AUTUMNALE BULB 12 [hp_X]/1 mL
INACTIVE INGREDIENTS: ALCOHOL; WATER

E08

Active Ingredients
Betula Verrucosa Leaf | 3X 6X
Bos Taurus Adrenal Gland | 4C
Bos Taurus Pituitarum Posterium | 7C
Calcarea Iodata | 8X 12X
Cocculus Indicus | 6X 9X 12X
Colchicum Autumnale | 6X 9X 12X
Eleuthero | 3X 6X 9X
European Hornbeam Flower | 12X 30X
European Olive Flower | 12X 30X
Gelsemium Sempervirens | 9X 12X 15X
Hypothalamus | 7C
Juniperus Communis Stem | 3X 6X 9X
Kali Carbonicum | 6X 9X 12X
Kali Phosphoricum | 4X 6X 9X 12X 30X
Lac Caninum | 10X 12X 15X
Nux Vomica | 6X 9X 12X 15X 30X
Passiflora Incarnata | 2X 4X 6X 12X
Phosphoricum Acidum | 4X 6X 9X 12X
Pyrenees Star Of Bethlehem Flowering Top | 12X 30X
Rhamnus Purshiana | 2X 4X 6X
Ribes Nigrum Flower Bud | 2X 4X 8X
Sarcolacticum Acidum | 3X 6X 9X 12X 30X
Sepia | 6X 9X 12X 15X 30X
Solidago Virgaurea | 3X 6X 9X
Sus Scrofa Pineal Gland | 4C
Tryptophan | 7C
Tyrosine | 7C

INDICATIONS AND USAGE

Uses:

For temporary relief of minor:

sleep disturbances*

headache*

fatigue*

menstrual irregularity*

lightheadedness*

yawning*

*Claims based on traditional homeopathic practice, not accepted medical evidence. Not FDA evaluated.

Warnings:

PREGNANCY OR BREAST FEEDING

If pregnant or breastfeeding, ask a health professional before use.

Do not use if clear seal over the cap is broken or missing.

Keep out of reach of children. In case of overdose, get medical help or contact a Poison Control Center right away.

Stop use and ask a doctor if sleep disturbances, headache, fatigue, menstrual irregularity, lightheadedness, yawning, or other symptoms do not improve within 7 days or are accompanied by fever.

Directions:

Adults & children ages 12 years and over: Take 10 drops under the tongue in the morning and evening, or as directed by your healthcare professional. Consult a physician for use in children under 12 years of age.

Inactive Ingredients

alcohol (20% by volume), distilled water

Distributed by Apex Energetics. Questions?1

16592 Hale Ave., Irvine, CA 92606, USA

PACKAGE LABEL

FUTUREPLEX® E08

ANTITOX®

BIOCLOCK REGULATOR™

Homeopathic Formula

Sleep Disturbances*

Headache* Fatigue*

1 fl oz (30 mL)

Alcohol 20% by Volume